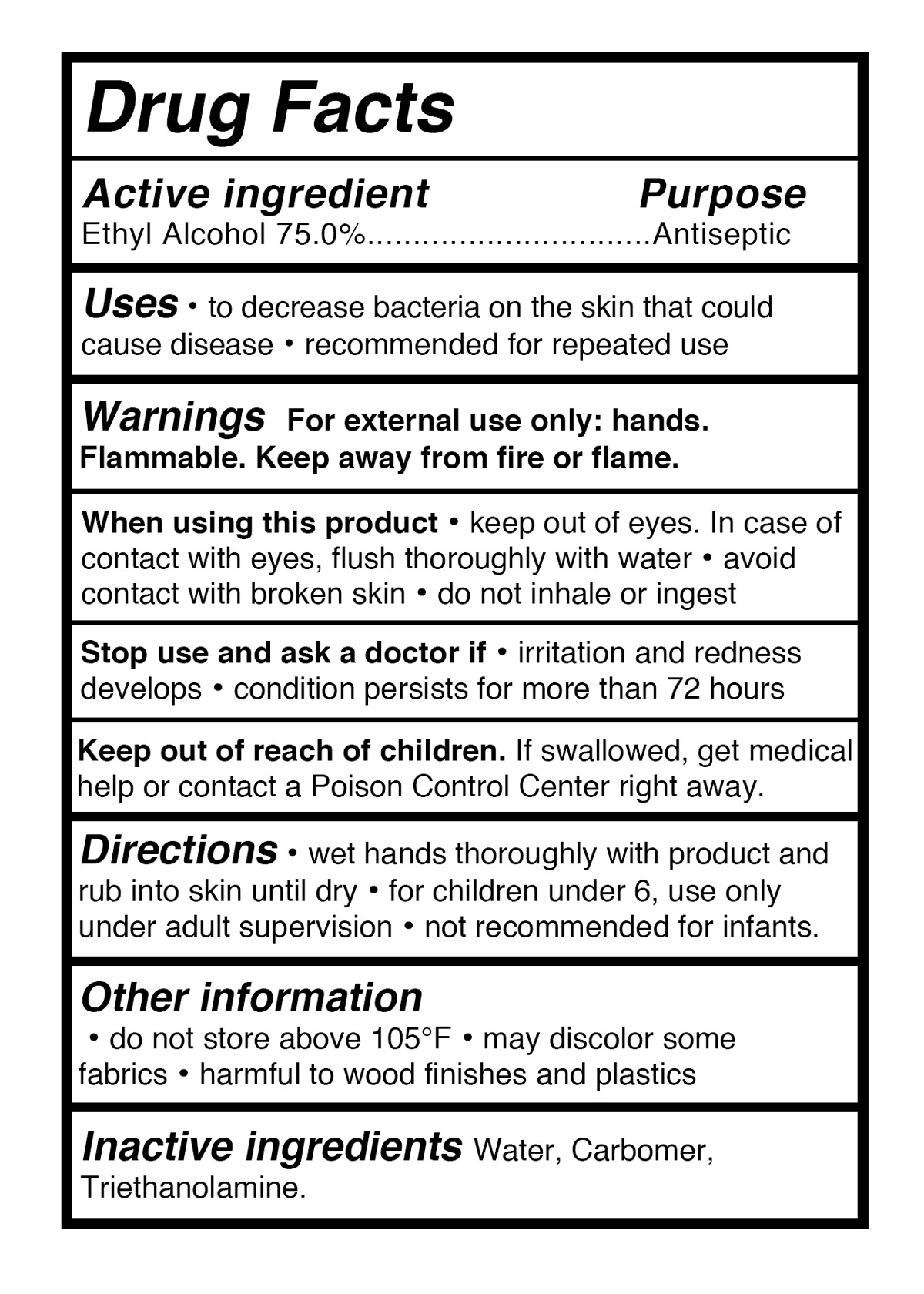 DRUG LABEL: Hand Sanitizer
NDC: 75468-001 | Form: GEL
Manufacturer: Henan Deyuanxiang Biological Technology Co.,  Ltd.
Category: otc | Type: HUMAN OTC DRUG LABEL
Date: 20200420

ACTIVE INGREDIENTS: ALCOHOL 75 mL/100 mL
INACTIVE INGREDIENTS: CARBOMER HOMOPOLYMER, UNSPECIFIED TYPE; TROLAMINE; WATER

75468-001 Hand Sanitizer

ACTIVE INGREDIENT

Ethyl Alcohol 75.0%

Purpose

Antiseptic

Use

●to decrease bacteria on the skin that could
cause disease ● recommended for repeated use

Warnings

For external use only: hands.
Flammable. Keep away from fire or flame.
When using this product●keep out of eyes. In case of
contact with eyes, flush thoroughly with water●avoid
contact with broken skin●do not inhale or ingest
Stop use and ask a doctor if●iritation and redness
develops●condition persists for more than 72 hours

Keep out of reach of children. If swallowed, get medical
help or contact a Poison Control Center right away.

Directions

●wet hands thoroughly with product and
rub into skin until dry●for children under 6, use only
under adult supervision●not recommended for infants.

Inactive ingredients

Water, Carbomer,Triethanolamine.

Other information

●Do not store above 105°F ●May discolor some
fabrics●Harmful to wood finishes and plastics